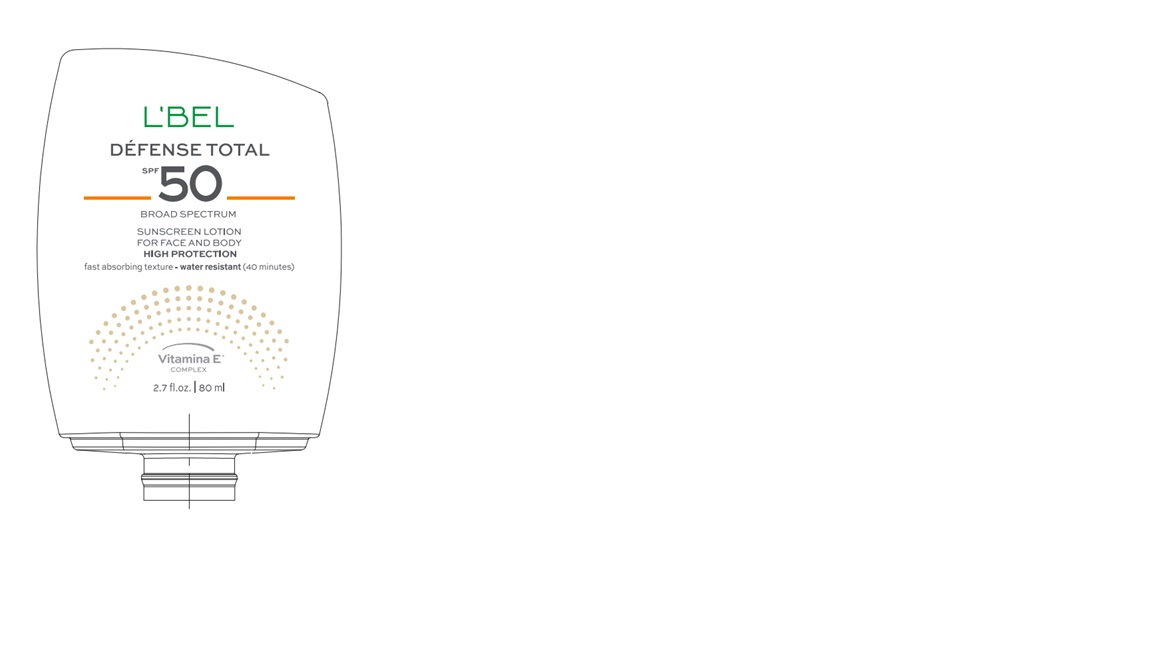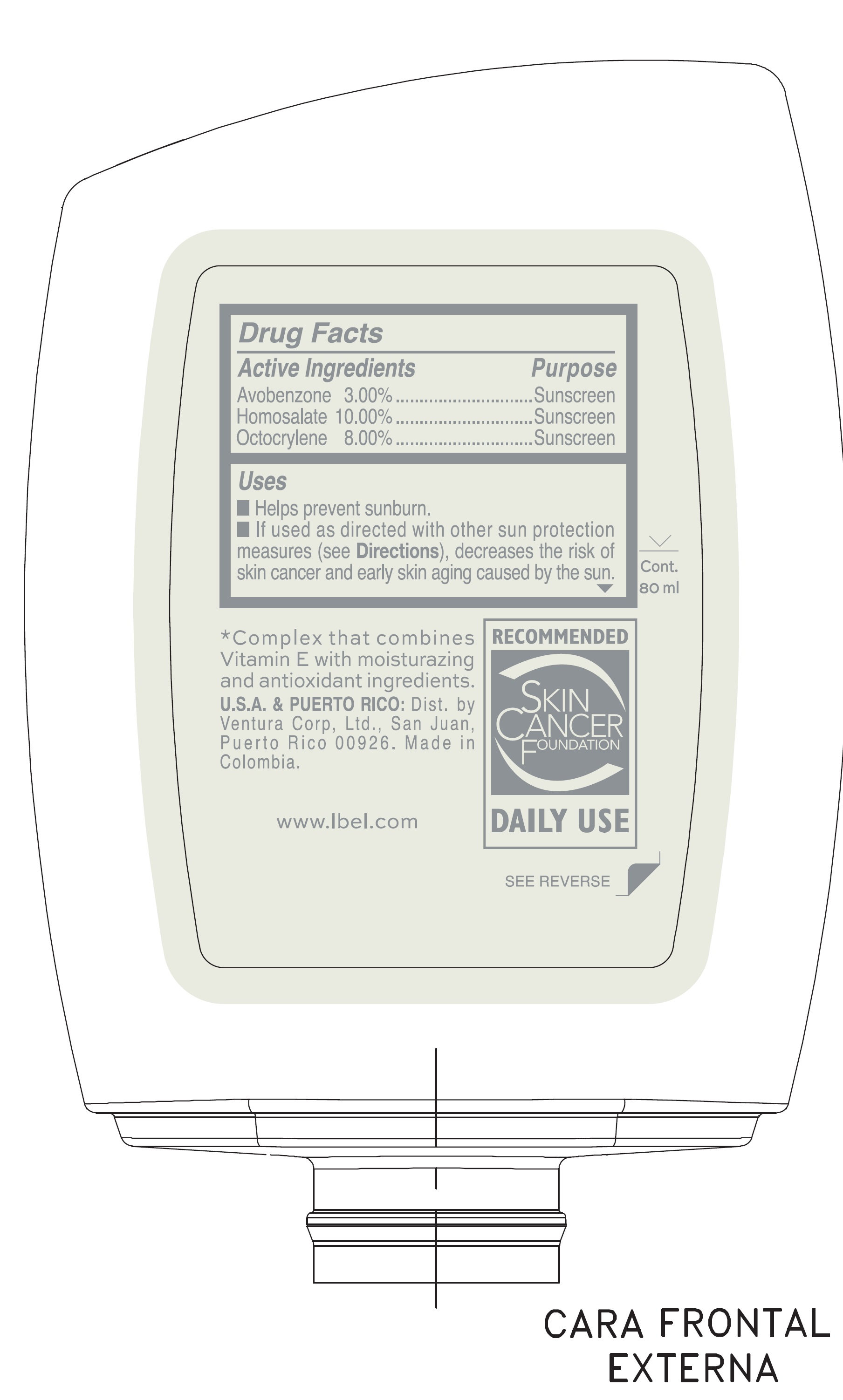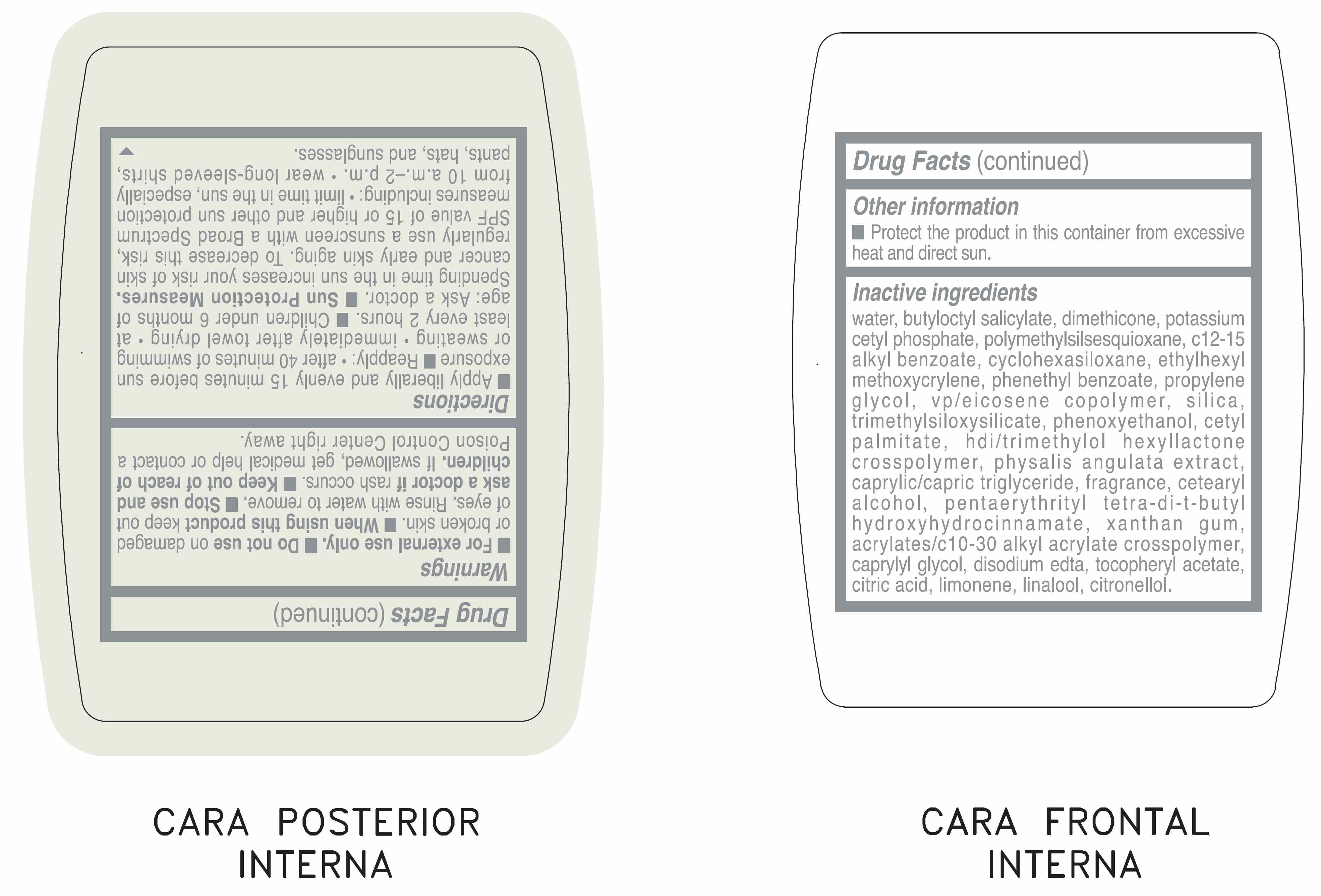 DRUG LABEL: LBEL DEFENSE TOTAL SUNSCREEN FOR FACE AND BODY SPF 50
NDC: 14141-331 | Form: EMULSION
Manufacturer: BEL STAR SA
Category: otc | Type: HUMAN OTC DRUG LABEL
Date: 20250620

ACTIVE INGREDIENTS: AVOBENZONE 30 mg/1 mL; HOMOSALATE 100 mg/1 mL; OCTOCRYLENE 80 mg/1 mL
INACTIVE INGREDIENTS: WATER; BUTYLOCTYL SALICYLATE; SILICON DIOXIDE; DIMETHICONE; CYCLOMETHICONE 6; POTASSIUM CETYL PHOSPHATE; POLYMETHYLSILSESQUIOXANE (4.5 MICRONS); ALKYL (C12-15) BENZOATE; ETHYLHEXYL METHOXYCRYLENE; PHENETHYL BENZOATE; PHENOXYETHANOL; PROPYLENE GLYCOL; VINYLPYRROLIDONE/EICOSENE COPOLYMER; CETYL PALMITATE; HEXAMETHYLENE DIISOCYANATE/TRIMETHYLOL HEXYLLACTONE CROSSPOLYMER; PHYSALIS ANGULATA; MEDIUM-CHAIN TRIGLYCERIDES; CETOSTEARYL ALCOHOL; PENTAERYTHRITOL TETRAKIS(3-(3,5-DI-TERT-BUTYL-4-HYDROXYPHENYL)PROPIONATE); XANTHAN GUM; CARBOMER COPOLYMER TYPE B (ALLYL PENTAERYTHRITOL CROSSLINKED); CAPRYLYL GLYCOL; EDETATE DISODIUM ANHYDROUS; ALPHA-TOCOPHEROL ACETATE; TRIMETHYLSILOXYSILICATE (M/Q 0.8-1.0); CITRIC ACID MONOHYDRATE; LIMONENE, (+)-; LINALOOL, (+)-; .BETA.-CITRONELLOL, (+/-)-

LBEL DEFENSE TOTAL SUNSCREEN FOR FACE AND BODY SPF 50

Active Ingredients

Avobenzone 3.00%

Homosalate 10.00%

Octocrylene 8.00%

Purpose

Sunscreen

Uses

- Helps prevent sunburn.
- If used as directed with other sun protection measures (see Directions), decreases the risk of skin cancer and early skin aging caused by the sun.

Warnings

- For external use only.

Do not use

on damaged or broken skin.

When using this product

keep out of eyes. Rinse with water to remove.

Stop use and ask a doctor if

rash occurs.

Keep out of reach of children.

If swallowed, get medical help or contact a Poison Control Center right away.

Directions

- Apply liberally and evenly 15 minutes before sun exposure.
- Reapply:
- after 40 minutes of swimming or sweating
- immediately after towel drying
- at least every 2 hours
- Children under 6 months of age: Ask a doctor
- Sun Protection Measures. Spending time in the sun increases your risk of skin cancer and early skin aging. To decrease this risk, regularly use a sunscreen with a Broad Spectrum SPF value of 15 or higher and other sun protection measures including:
- limit time in the sun, especially from 10 a.m. - 2 p.m.
- wear long sleeved shirts, pants, hats, and sunglasses.

Other information

Protect the product in this container from excessive heat and direct sun.

Inactive ingredients

WATER, BUTYLOCTYL SALICYLATE, DIMETHICONE, POTASSIUM CETYL PHOSPHATE, POLYMETHYLSILSESQUIOXANE, C12-15 ALKYL BENZOATE, CYCLOHEXASILOXANE, ETHYLHEXYL METHOXYCRYLENE, PHENETHYL BENZOATE, PROPYLENE GLYCOL, VP/EICOSENE COPOLYMER, SILICA, TRIMETHYLSILOXYSILICATE, PHENOXYETHANOL, CETYL PALMITATE, HDI/TRIMETHYLOL HEXYLLACTONE CROSSPOLYMER, PHYSALIS ANGULATA EXTRACT, CAPRYLIC/CAPRIC TRIGLYCERIDE, FRAGRANCE, CETEARYL ALCOHOL, PENTAERYTHRITYL TETRA-DI-T-BUTYL HYDROXYHYDROCINNAMATE, XANTHAN GUM, ACRYLATES/C10-30 ALKYL ACRYLATE CROSSPOLYMER, CAPRYLYL GLYCOL, DISODIUM EDTA, TOCOPHERYL ACETATE, CITRIC ACID, LIMONENE, LINALOOL, CITRONELLOL.

Company Information

U.S.A. & PUERTO RICO: Dist. by Ventura Corp, Ltd., San Juan, Puerto Rico 00926. Made in Colombia.